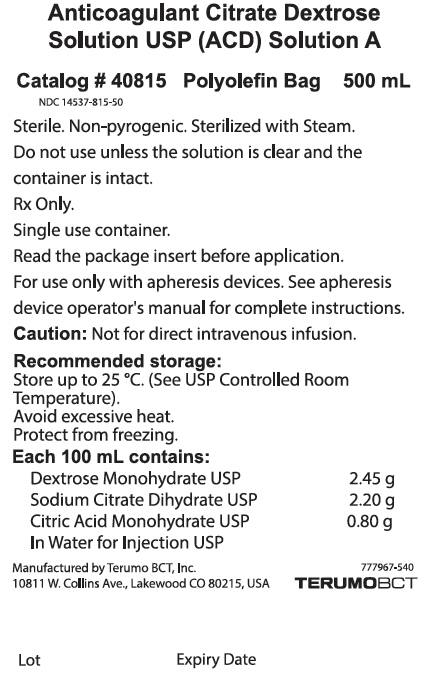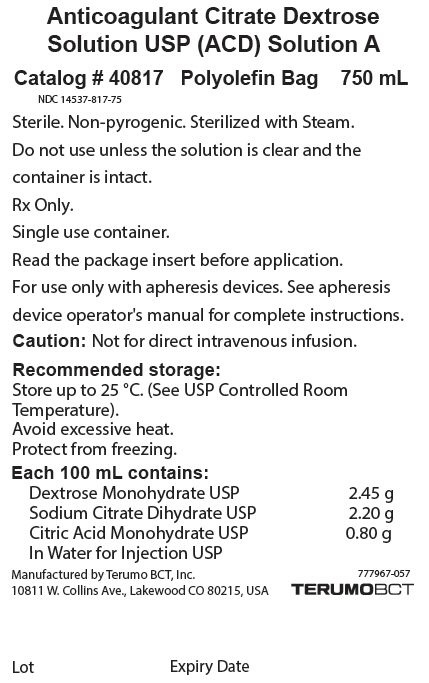 DRUG LABEL: ACD 
NDC: 14537-817 | Form: INJECTION, SOLUTION
Manufacturer: Terumo BCT, Ltd.
Category: prescription | Type: HUMAN PRESCRIPTION DRUG LABEL
Date: 20250122

ACTIVE INGREDIENTS: Citric Acid Monohydrate 0.8 g/100 mL; Dextrose Monohydrate 2.45 g/100 mL; Trisodium Citrate Dihydrate 2.2 g/100 mL
INACTIVE INGREDIENTS: Water

HIGHLIGHTS OF PRESCRIBING INFORMATION

These highlights do not include all the information needed to use ANTICOAGULANT CITRATE DEXTROSE SOLUTION USP (ACD) SOLUTION A safely and effectively. See full prescribing information for ANTICOAGULANT CITRATE DEXTROSE SOLUTION USP (ACD) SOLUTION A.
ANTICOAGULANT CITRATE DEXTROSE SOLUTION USP (ACD) SOLUTION A
Sterile Fluid
Polyolefin Bag
Initial U.S. Approval: 1987

1 INDICATIONS AND USAGE

ANTICOAGULANT CITRATE DEXTROSE SOLUTION USP (ACD) SOLUTION A is an anticoagulant for blood collection for use only with apheresis devices. (1)

2 DOSAGE AND ADMINISTRATION

- ANTICOAGULANT CITRATE DEXTROSE SOLUTION USP (ACD) SOLUTION A is added to tubing sets during apheresis procedures. (2)
- ANTICOAGULANT CITRATE DEXTROSE SOLUTION USP (ACD) SOLUTION A may only be used with apheresis devices. For instructions on the use of the solution see the apheresis device operator's manual. (2.1)
- Follow the directions for connecting the ANTICOAGULANT CITRATE DEXTROSE SOLUTION USP (ACD) SOLUTION A bag to the apheresis system. (2.2)

3 DOSAGE FORMS AND STRENGTHS

- 500 mL or 750 mL sterile fluid in polyolefin bag. (3)

4 CONTRAINDICATIONS

- DO NOT INFUSE ANTICOAGULANT CITRATE DEXTROSE SOLUTION USP (ACD) SOLUTION A DIRECTLY TO THE PATIENTS. (4)

5 WARNINGS AND PRECAUTIONS

- Verify that the ANTICOAGULANT CITRATE DEXTROSE SOLUTION USP (ACD) SOLUTION A has been securely attached to the Anticoagulant (AC) line on the system tubing set. Use aseptic technique throughout all procedures to ensure donor safety and quality. (5)

6 ADVERSE REACTIONS

Citrate reactions or toxicity may occur with the infusion and return of blood containing citrate anticoagulant. The recipient of the blood containing citrate should be monitored for the signs and symptoms of citrate toxicity. (6)

To report SUSPECTED ADVERSE REACTIONS, contact Terumo BCT, Inc. at 1-877-339-4228 or FDA at 1-800-FDA-1088 or www.fda.gov/medwatch.

8 USE IN SPECIFIC POPULATIONS

ANTICOAGULANT CITRATE DEXTROSE SOLUTION USP (ACD) SOLUTION A has not been studied in controlled clinical trials with specific populations.

FULL PRESCRIBING INFORMATION

1 INDICATIONS AND USAGE

ANTICOAGULANT CITRATE DEXTROSE SOLUTION USP (ACD) SOLUTION A is an anticoagulant for blood collection for use only with apheresis devices. [See Dosage and Administration (2).]

2 DOSAGE AND ADMINISTRATION

2.1 General Dosing Information

ANTICOAGULANT CITRATE DEXTROSE SOLUTION USP (ACD) SOLUTION A is added to tubing sets during apheresis procedures. The solution is connected to the tubing set in an apheresis collection. The recommended dose is determined by the apheresis device and metered into the tubing set by the apheresis device. It is not intended for direct intravenous infusion.

For instructions on the use of the solution with the apheresis device and tubing set, see the device operator's manual.

2.2 Administration

- Ensure solution is the ANTICOAGULANT CITRATE DEXTROSE SOLUTION USP (ACD) SOLUTION A and is within the expiration date.
- Inspect the bag. Do not use if the container is damaged, leaking or if there is any visible sign of deterioration.
- Use only if solution is clear and free of particulate matter.
- Protect from sharp objects.

Directions for Connecting the ANTICOAGULANT CITRATE DEXTROSE SOLUTION USP (ACD) SOLUTION A bag to the apheresis device.

At the prompt to connect anticoagulant to the apheresis device tubing set:

1. Remove the overwrap by pulling down at notch, and remove the ANTICOAGULANT CITRATE DEXTROSE SOLUTION USP (ACD) SOLUTION A bag.
2. Before use, perform the following checks [See Warnings and Precautions (5).]:
  - Check for leaks by gently squeezing the bag. If leaks are found, discard the bag.
  - Ensure that the solution is the ANTICOAGULANT CITRATE DEXTROSE SOLUTION USP (ACD) SOLUTION A and is within the expiration date.
  - Inspect the solution in adequate light. Bags showing cloudiness, haze, or particulate matter should not be used.
3. Remove the protective cap from the port on the bag.
4. Connect the bag to the apheresis device tubing set using aseptic technique and hang the solution.
5. Break the frangible connector. When you break frangible connectors, bend them in both directions to ensure that you break them completely. Failure to do so may result in restricted flow.
6. Proceed according to the apheresis device operator's manual.

Parenteral drug products should be inspected visually for particulate matter and discoloration prior to administration, whenever solution and container permit.

3 DOSAGE FORMS AND STRENGTHS

500 mL or 750 mL ANTICOAGULANT CITRATE DEXTROSE SOLUTION USP (ACD) SOLUTION A is a sterile solution in a polyolefin bag. Each 100 mL contains: (%w/v) Citric Acid, Monohydrate 0.8 g; Dextrose Monohydrate 2.45 g; Sodium Citrate Dihydrate 2.2 g; and Water for Injection.

4 CONTRAINDICATIONS

DO NOT INFUSE ANTICOAGULANT CITRATE DEXTROSE SOLUTION USP (ACD) SOLUTION A DIRECTLY TO THE PATIENTS.

5 WARNINGS AND PRECAUTIONS

- Verify that the ANTICOAGULANT CITRATE DEXTROSE SOLUTION USP (ACD) SOLUTION A has been securely attached to the Anticoagulant (AC) line on the system tubing set. Use aseptic technique throughout all procedures to ensure donor safety and quality.
- Do not reuse. Discard unused or partially used solution bags.

6 ADVERSE REACTIONS

Citrate reactions or toxicity may occur with the infusion and return of blood containing citrate anticoagulant. The recipient of the blood containing citrate should be monitored for the signs and symptoms of citrate toxicity. The signs and symptoms of citrate toxicity begin with paresthesia, a "tingling" sensation around the mouth or in the extremities, followed by severe reactions that are characterized by hypotension and possible cardiac arrhythmia. Citrate toxicity may occur more frequently in patients who are hypothermic, have impaired liver or renal function, or have low calcium levels because of an underlying disease.

8 USE IN SPECIFIC POPULATIONS

ANTICOAGULANT CITRATE DEXTROSE SOLUTION USP (ACD) SOLUTION A has not been adequately studied in controlled clinical trials with specific populations.

11 DESCRIPTION

ANTICOAGULANT CITRATE DEXTROSE SOLUTION USP (ACD) SOLUTION A is designed to be metered by an apheresis device in apheresis procedures, to prevent platelet activation and coagulation as blood moves throughout the extracorporeal unit (tubing set) in an apheresis procedure.

The solution is sterile and non-pyrogenic, and it contains no bacteriostatic or antimicrobial agents.

The formulas of the active ingredients are provided in Table 1.

Table 1: Active Ingredients
Ingredients | Molecular Formula | Molecular Weight
(%w/v) Citric Acid, Monohydrate | C6H8O7 | 192.12
Dextrose Monohydrate | C6H12O6 ∙ H2O | 198.17
Sodium Citrate Dihydrate | C6H9Na3O9 | 294.10
Water for Injection | H2O | 18.00

Each 100 mL of ANTICOAGULANT CITRATE DEXTROSE SOLUTION USP (ACD) SOLUTION A contains: (%w/v) Citric Acid, Monohydrate 0.8 g; Dextrose Monohydrate 2.45 g; Sodium Citrate Dihydrate 2.2 g; and Water for Injection.

The polyolefin bag is not made with natural rubber latex or PVC.

The bag is made from a multilayered film. It contains materials that have been tested to demonstrate the suitability of the container for storing pharmaceutical solutions. The solution contact layer is an elasticized polyolefin. The bag is nontoxic and biologically inert. The bag-solution unit is a closed system and is not dependent upon entry of external air during administration. The bag is overwrapped to provide protection from the physical environment and to provide an additional moisture barrier when necessary.

12 CLINICAL PHARMACOLOGY

12.1 Mechanism of Action

ANTICOAGULANT CITRATE DEXTROSE SOLUTION USP (ACD) SOLUTION A acts as an extracorporeal anticoagulant by binding the free calcium in the blood. Calcium is a necessary co-factor to several steps in the clotting cascade. The following ingredients are key components of the solution:

- Citric acid for pH regulation
- Sodium Citrate anticoagulates
- Dextrose for isotonicity

This solution has no pharmacological effect.

16 HOW SUPPLIED/STORAGE AND HANDLING

ANTICOAGULANT CITRATE DEXTROSE SOLUTION USP (ACD) SOLUTION A is a clear solution supplied in sterile and non-pyrogenic polyolefin bags. The 750 mL bags are packaged 12 bags per case. The 500 mL bags are packaged 18 bags per case.

SIZE | CATALOG NUMBER | NDC NUMBER
500 mL | 40815 | 14537-815-50
750 mL | 40817 | 14537-817-75

STORAGE

Store up to 25 °C [See USP Controlled Room Temperature].
Avoid excessive heat. Protect from freezing.

Issued: (August 2017)

Manufactured by
Terumo BCT, Inc.
Lakewood, CO 80215

PRINCIPAL DISPLAY PANEL - 750 mL Bag Label

Anticoagulant Citrate Dextrose
Solution USP (ACD) Solution A

Catalog # 40817
Polyolefin Bag
750 mL

NDC 14537-817-75

Sterile. Non-pyrogenic. Sterilized with Steam.

Do not use unless the solution is clear and the
container is intact.

Rx Only.

Single use container.

Read the package insert before application.

For use only with apheresis devices. See apheresis
device operator's manual for complete instructions.

Caution: Not for direct intravenous infusion.

Recommended storage:
Store up to 25 °C. (See USP Controlled Room
Temperature).
Avoid excessive heat.
Protect from freezing.

Each 100 mL contains:
Dextrose Monohydrate USP
2.45 g
Sodium Citrate Dihydrate USP
2.20 g
Citric Acid Monohydrate USP
0.80 g
In Water for Injection USP

Manufactured by Terumo BCT, Inc.
10811 W. Collins Ave., Lakewood CO 80215, USA

777967-057
TERUMOBCT

Lot
Expiry Date

PRINCIPAL DISPLAY PANEL - 500 mL Bag Label

Anticoagulant Citrate Dextrose
Solution USP (ACD) Solution A

Catalog # 40815
Polyolefin Bag
500 mL

NDC 14537-815-50

Sterile. Non-pyrogenic. Sterilized with Steam.

Do not use unless the solution is clear and the
container is intact.

Rx Only.

Single use container.

Read the package insert before application.

For use only with apheresis devices. See apheresis
device operator's manual for complete instructions.

Caution: Not for direct intravenous infusion.

Recommended storage:
Store up to 25 °C. (See USP Controlled Room
Temperature).
Avoid excessive heat.
Protect from freezing.

Each 100 mL contains:
Dextrose Monohydrate USP
2.45 g
Sodium Citrate Dihydrate USP
2.20 g
Citric Acid Monohydrate USP
0.80 g
In Water for Injection USP

Manufactured by Terumo BCT, Inc.
10811 W. Collins Ave., Lakewood CO 80215, USA

777967-540
TERUMOBCT

Lot
Expiry Date